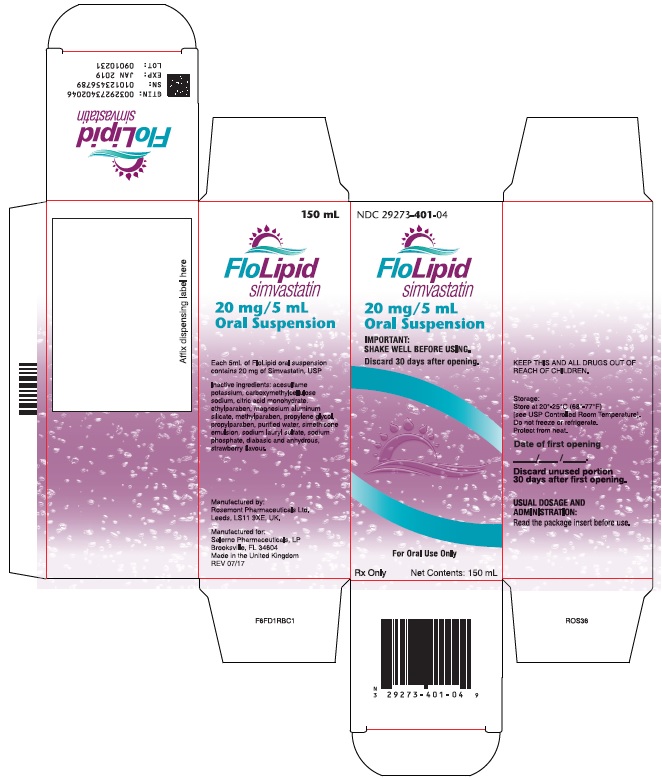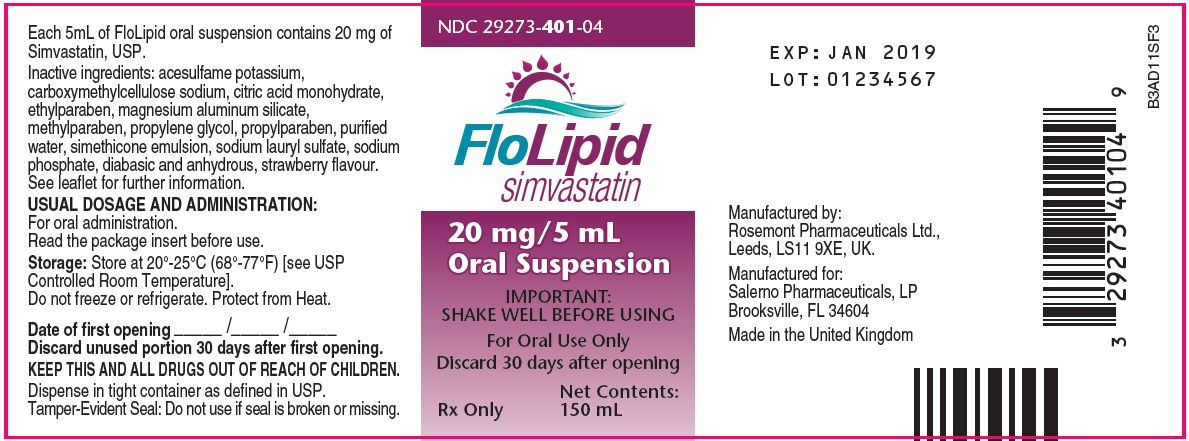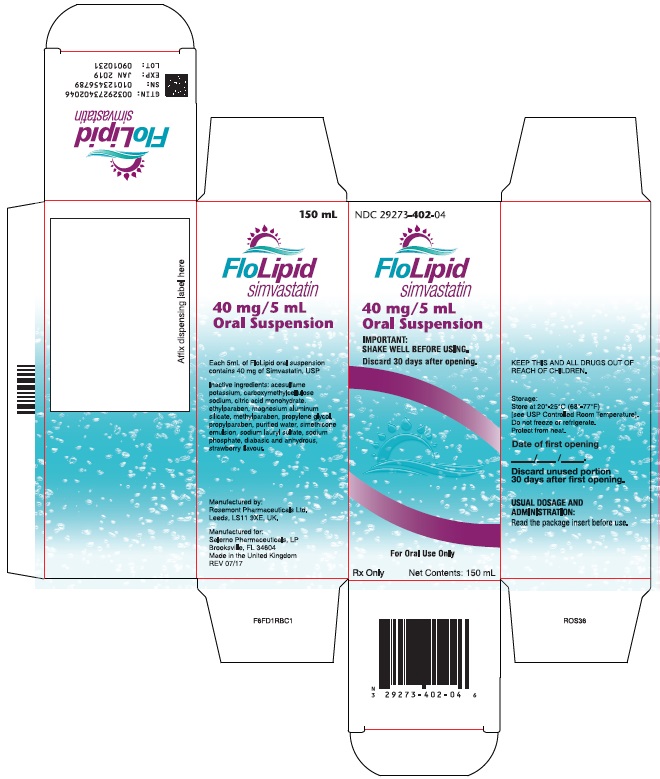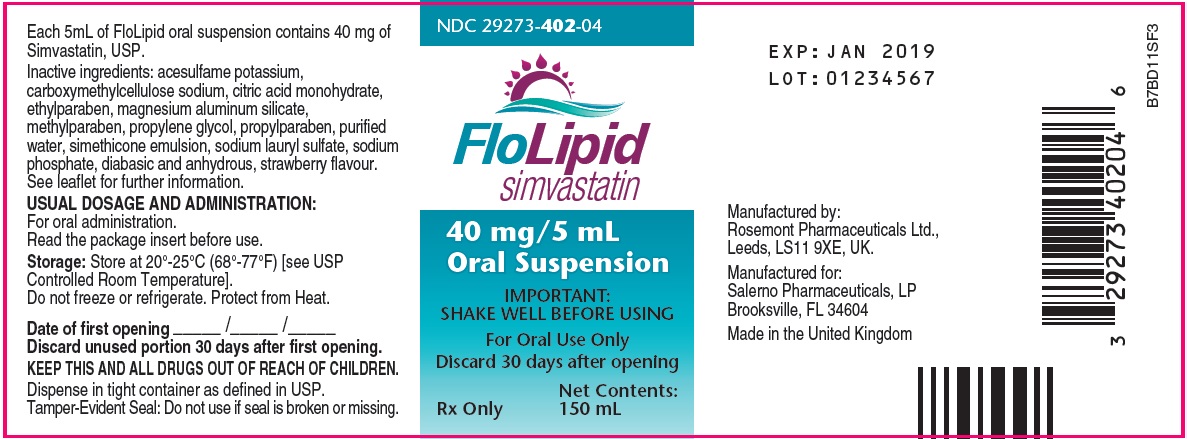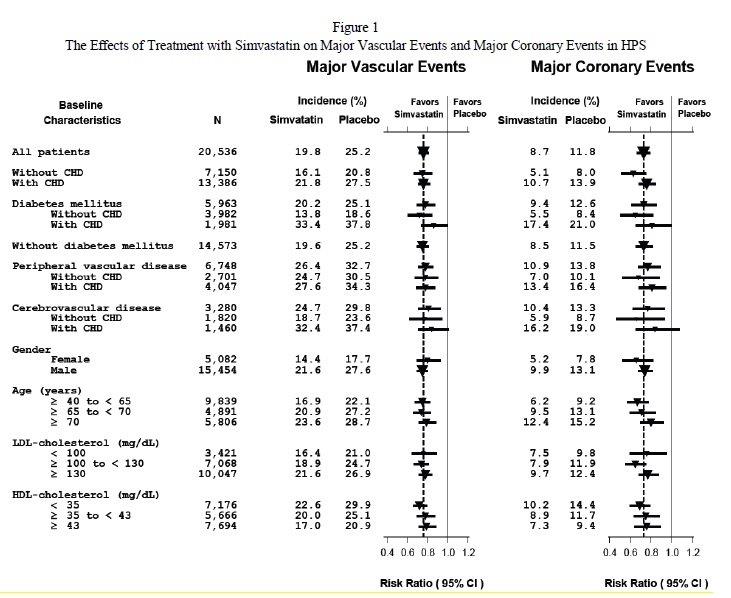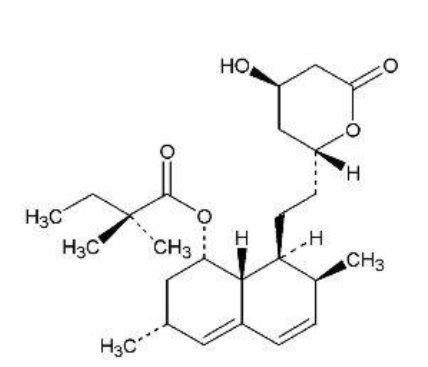 DRUG LABEL: FloLipid
NDC: 29273-401 | Form: SUSPENSION
Manufacturer: Salerno Pharmaceuticals Co.
Category: prescription | Type: HUMAN PRESCRIPTION DRUG LABEL
Date: 20230209

ACTIVE INGREDIENTS: SIMVASTATIN 20 mg/5 mL
INACTIVE INGREDIENTS: PROPYLENE GLYCOL; PROPYLPARABEN; WATER; DIMETHICONE; SODIUM LAURYL SULFATE; SODIUM PHOSPHATE, DIBASIC, ANHYDROUS; ACESULFAME POTASSIUM; CARBOXYMETHYLCELLULOSE SODIUM, UNSPECIFIED FORM; CITRIC ACID MONOHYDRATE; ETHYLPARABEN; MAGNESIUM ALUMINUM SILICATE; METHYLPARABEN

HIGHLIGHTS OF PRESCRIBING INFORMATION

These highlights do not include all the information needed to use FLOLIPID safely and effectively. See full prescribing information for FLOLIPID.
FLOLIPID (simvastatin) oral suspension
Initial U.S. Approval: 1991

RECENT MAJOR CHANGES

Immune-Mediated Necrotizing Myopathy (5.2) | 06/2020

1 INDICATIONS AND USAGE

FLOLIPID is an HMG-CoA reductase inhibitor (statin) indicated as an adjunctive therapy to diet to:

- Reduce the risk of total mortality by reducing CHD deaths and reduce the risk of non-fatal myocardial infarction, stroke, and the need for revascularization procedures in patients at high risk of coronary events. (1.1)
- Reduce elevated total-C, LDL-C, Apo B, TG and increase HDL-C in patients with primary hyperlipidemia (heterozygous familial and nonfamilial) and mixed dyslipidemia. (1.2)
- Reduce elevated TG in patients with hypertriglyceridemia and reduce TG and VLDL-C in patients with primary dysbetalipoproteinemia. (1.2)
- Reduce total-C and LDL-C in adult patients with homozygous familial hypercholesterolemia. (1.2)
- Reduce elevated total-C, LDL-C, and Apo B in boys and postmenarchal girls, 10 to 17 years of age with heterozygous familial hypercholesterolemia after failing an adequate trial of diet therapy. (1.2, 1.3)

Limitations of Use

Simvastatin has not been studied in Fredrickson Types I and V dyslipidemias. (1.4)

2 DOSAGE AND ADMINISTRATION

- Dose range is 5 to 40 mg/day. (2.1)
- Shake bottle well for at least 20 seconds before using. (2.1)
- Measure FLOLIPID with an accurate measuring device. (2.1)
- Recommended usual starting dose is 10 or 20 mg once a day in the evening on an empty stomach. (2.1)
- Recommended to use FLOLIPID 40 mg/5 mL for dosages greater than or equal to 40 mg. (2.1)
- Recommended starting dose for patients at high risk of CHD is 40 mg/day. (2.1)
- Due to the increased risk of myopathy, including rhabdomyolysis, use of the 80-mg dose of FLOLIPID should be restricted to patients who have been taking simvastatin 80 mg chronically (e.g., for 12 months or more) without evidence of muscle toxicity. (2.2)
- Patients who are currently tolerating the 80-mg dose of FLOLIPID who need to be initiated on an interacting drug that is contraindicated or is associated with a dose cap for simvastatin should be switched to an alternative statin with less potential for the drug-drug interaction. (2.2)
- Due to the increased risk of myopathy, including rhabdomyolysis, associated with the 80-mg dose of FLOLIPID, patients unable to achieve their LDL-C goal utilizing the 40-mg dose of FLOLIPID should not be titrated to the 80-mg dose, but should be placed on alternative LDL-Clowering treatment(s) that provides greater LDL-C lowering. (2.2)
- Adolescents (10 to 17 years of age) with HeFH: starting dose is 10 mg/day; maximum recommended dose is 40 mg/day. (2.5)

3 DOSAGE FORMS AND STRENGTHS

Oral suspension: 20 mg/5 mL (4 mg per mL) and 40 mg/5 mL (8 mg per mL) (3)

4 CONTRAINDICATIONS

- Concomitant administration of strong CYP3A4 inhibitors. (4, 5.1)
- Concomitant administration of gemfibrozil, cyclosporine, or danazol. (4, 5.1)
- Hypersensitivity to any component of this medication. (4, 6.2)
- Active liver disease, which may include unexplained persistent elevations in hepatic transaminase levels. (4, 5.3)
- Women who are pregnant or may become pregnant. (4, 8.1)
- Nursing mothers. (4, 8.3)

5 WARNINGS AND PRECAUTIONS

- Patients should be advised of the increased risk of myopathy including rhabdomyolysis with the 80-mg dose. (5.1)
- Skeletal muscle effects (e.g., myopathy and rhabdomyolysis): Risks increase with the higher doses and concomitant use of certain medicines. Predisposing factors include advanced age (≥65), female gender, uncontrolled hypothyroidism, and renal impairment. Rare cases of rhabdomyolysis with acute renal failure secondary to myoglobinuria have been reported. (4, 5.1, 8.5, 8.6)
- Patients should be advised to report promptly any unexplained and/or persistent muscle pain, tenderness, or weakness. FLOLIPID therapy should be discontinued immediately if myopathy is diagnosed or suspected. See Drug Interaction table. (5.1)
- Immune-Mediated Necrotizing Myopathy (IMNM): There have been rare reports of IMNM, an autoimmune myopathy, associated with statin use. IMNM is characterized by: proximal muscle weakness and elevated serum creatine kinase, which persist despite discontinuation of statin treatment; positive anti-HMG CoA reductase antibody; muscle biopsy showing necrotizing myopathy; and improvement with immunosuppressive agents. (5.2)
- Liver enzyme abnormalities: Persistent elevations in hepatic transaminases can occur. Check liver enzyme tests before initiating therapy and as clinically indicated thereafter. (5.3)

6 ADVERSE REACTIONS

Most common adverse reactions (incidence ≥5.0%) are: upper respiratory infection, headache, abdominal pain, constipation, and nausea. (6.1)

To report SUSPECTED ADVERSE REACTIONS, contact Salerno at 1-352-797-5227 or FDA at 1-800-FDA-1088 or www.fda.gov/medwatch.

7 DRUG INTERACTIONS

Drug Interactions Associated with Increased Risk of Myopathy/Rhabdomyolysis (2.3, 2.4, 4, 5.1, 7.1, 7.2, 7.3, 12.3)

Interacting Agents | Prescribing Recommendations
Strong CYP3A4 inhibitors (e.g., itraconazole, ketoconazole, posaconazole, voriconazole, erythromycin, clarithromycin, telithromycin, HIV protease inhibitors, boceprevir, telaprevir, nefazodone, cobicistat-containing products), gemfibrozil, cyclosporine, danazol | Contraindicated with simvastatin
Verapamil, diltiazem, dronedarone | Do not exceed 10 mg simvastatin daily
Amiodarone, amlodipine, ranolazine | Do not exceed 20 mg simvastatin daily
Lomitapide | For patients with HoFH, do not exceed 20 mg simvastatin daily [For patients with HoFH who have been taking 80 mg simvastatin chronically (e.g., for 12 months or more) without evidence of muscle toxicity, do not exceed 40 mg simvastatin when taking lomitapide.]
Grapefruit juice | Avoid grapefruit juice

- Other Lipid-lowering Medications: Use with other fibrate products or lipid-modifying doses (≥1 g/day) of niacin increases the risk of adverse skeletal muscle effects. Caution should be used when prescribing with simvastatin. (5.1, 7.2, 7.4).
- Coumarin anticoagulants: Concomitant use with FLOLIPID prolongs INR. Achieve stable INR prior to starting FLOLIPID. Monitor INR frequently until stable upon initiation or alteration of FLOLIPID therapy. (7.6)

8 USE IN SPECIFIC POPULATIONS

- Severe renal impairment: patients should be started at 5 mg/day and be closely monitored. (2.6, 8.6)

FULL PRESCRIBING INFORMATION

1 INDICATIONS AND USAGE

Therapy with lipid-altering agents should be only one component of multiple risk factor intervention in individuals at significantly increased risk for atherosclerotic vascular disease due to hypercholesterolemia. Drug therapy is indicated as an adjunct to diet when the response to a diet restricted in saturated fat and cholesterol and other nonpharmacologic measures alone has been inadequate. In patients with coronary heart disease (CHD) or at high risk of CHD, FLOLIPID can be started simultaneously with diet.

1.1 Reductions in Risk of CHD Mortality and Cardiovascular Events

In patients at high risk of coronary events because of existing coronary heart disease, diabetes, peripheral vessel disease, history of stroke or other cerebrovascular disease, FLOLIPID is indicated to:

- Reduce the risk of total mortality by reducing CHD deaths.
- Reduce the risk of non-fatal myocardial infarction and stroke.
- Reduce the need for coronary and non-coronary revascularization procedures.

1.2 Hyperlipidemia

FLOLIPID is indicated to:

- Reduce elevated total cholesterol (total-C), low-density lipoprotein cholesterol (LDL-C), apolipoprotein B (Apo B), and triglycerides (TG), and to increase high-density lipoprotein cholesterol (HDL-C) in patients with primary hyperlipidemia (Fredrickson type IIa, heterozygous familial and nonfamilial) or mixed dyslipidemia (Fredrickson type IIb).
- Reduce elevated TG in patients with hypertriglyceridemia (Fredrickson type IV hyperlipidemia).
- Reduce elevated TG and VLDL-C in patients with primary dysbetalipoproteinemia (Fredrickson type III hyperlipidemia).
- Reduce total-C and LDL-C in patients with homozygous familial hypercholesterolemia (HoFH) as an adjunct to other lipidlowering treatments (e.g., LDL apheresis) or if such treatments are unavailable.

1.3 Adolescent Patients with Heterozygous Familial Hypercholesterolemia (HeFH)

FLOLIPID is indicated as an adjunct to diet to reduce total-C, LDL-C, and Apo B levels in adolescent boys and girls who are at least one year post-menarche, 10 to 17 years of age, with HeFH, if after an adequate trial of diet therapy the following findings are present:

1. LDL cholesterol remains ≥190 mg/dL; or

2. LDL cholesterol remains ≥160 mg/dL and

- There is a positive family history of premature cardiovascular disease (CVD) or
- Two or more other CVD risk factors are present in the adolescent patient.

The minimum goal of treatment in pediatric and adolescent patients is to achieve a mean LDL-C <130 mg/dL. The optimal age at which to initiate lipid-lowering therapy to decrease the risk of symptomatic adulthood CAD has not been determined.

1.4 Limitations of Use

FLOLIPID has not been studied in conditions where the major abnormality is elevation of chylomicrons (i.e., hyperlipidemia Fredrickson types I and V).

2 DOSAGE AND ADMINISTRATION

2.1 Recommended Dosing

The usual dosage range is 5 to 40 mg/day. FLOLIPID should be taken in the evening on an empty stomach [see Clinical Pharmacology (12.3)] . Shake bottle well for at least 20 seconds before using. In patients with CHD or at high risk of CHD, FLOLIPID can be started simultaneously with diet. The recommended usual starting dose is 10 or 20 mg once a day. For patients at high risk for a CHD event due to existing CHD, diabetes, peripheral vessel disease, history of stroke or other cerebrovascular disease, the recommended starting dose is 40 mg/day. It is recommended to use FLOLIPID 40 mg/5 mL for dosages greater than or equal to 40 mg. Lipid determinations should be performed after 4 weeks of therapy and periodically thereafter.

Patients should be advised to measure FLOLIPID with an accurate measuring device. A household teaspoon is not an accurate measuring device and could lead to overdosage. A pharmacist can recommend an appropriate measuring device and can provide instructions for measuring the correct dose.

2.2 Restricted Dosing for 80 mg

Due to the increased risk of myopathy, including rhabdomyolysis, particularly during the first year of treatment, use of an 80-mg dose of FLOLIPID should be restricted to patients who have been taking FLOLIPID 80 mg chronically (e.g., for 12 months or more) without evidence of muscle toxicity [see Warnings and Precautions (5.1)] .

Patients who are currently tolerating the an 80-mg dose of FLOLIPID who need to be initiated on an interacting drug that is contraindicated or is associated with a dose cap for simvastatin should be switched to an alternative statin with less potential for the drug-drug interaction.

Due to the increased risk of myopathy, including rhabdomyolysis, associated with an 80-mg dose of FLOLIPID, patients unable to achieve their LDL-C goal utilizing the 40-mg dose of FLOLIPID should not be titrated to an 80-mg dose, but should be placed on alternative LDL-C-lowering treatment(s) that provides greater LDL-C lowering.

2.3 Coadministration with Other Drugs

Patients taking Verapamil, Diltiazem, or Donedarone

- The dose of FLOLIPID should not exceed 10 mg/day [see Warnings and Precautions (5.1), Drug Interactions (7.3), and Clinical Pharmacology (12.3)] .

Patients taking Amiodarone, Amlodipine or Ranolazine

- The dose of FLOLIPID should not exceed 20 mg/day [see Warnings and Precautions (5.1), Drug Interactions (7.3), and Clinical Pharmacology (12.3)].

2.4 Patients with Homozygous Familial Hypercholesterolemia

The recommended dosage is 40 mg/day in the evening on an empty stomach [see Dosage and Administration, Restricted Dosing for 80 mg (2.2)]. FLOLIPID should be used as an adjunct to other lipid-lowering treatments (e.g., LDL apheresis) in these patients or if such treatments are unavailable.

Simvastatin exposure is approximately doubled with concomitant use of lomitapide; therefore, the dose of FLOLIPID should be reduced by 50% if initiating lomitapide. FLOLIPID dosage should not exceed 20 mg/day (or 40 mg/day for patients who have previously taken 80 mg/day of simvastatin chronically, e.g., for 12 months or more, without evidence of muscle toxicity) while taking lomitapide.

2.5 Adolescents (10 to 17 years of age) with Heterozygous Familial Hypercholesterolemia

The recommended usual starting dose is 10 mg once a day in the evening on an empty stomach. The recommended dosing range is 10 to 40 mg/day; the maximum recommended dose is 40 mg/day. Doses should be individualized according to the recommended goal of therapy [see NCEP Pediatric Panel Guidelines [National Cholesterol Education Program (NCEP): Highlights of the Report of the Expert Panel on Blood Cholesterol Levels in Children and Adolescents. Pediatrics. 89(3):495-501.1992] and Clinical Studies (14.2)] . Adjustments should be made at intervals of 4 weeks or more.

2.6 Patients with Renal Impairment

Because simvastatin does not undergo significant renal excretion, modification of dosage should not be necessary in patients with mild to moderate renal impairment. However, caution should be exercised when FLOLIPID is administered to patients with severe renal impairment; such patients should be started at 5 mg/day and be closely monitored [see Warnings and Precautions (5.1) and Clinical Pharmacology (12.3)].

2.7 Chinese Patients Taking Lipid-Modifying Doses (greater than or equal to 1 g/day Niacin) of Niacin-Containing Products

Because of an increased risk for myopathy in Chinese patients taking simvastatin 40 mg coadministered with lipid-modifying doses (greater than or equal to 1 g/day niacin) of niacin-containing products, caution should be used when treating Chinese patients with simvastatin doses exceeding 20 mg/day coadministered with lipid-modifying doses of niacin-containing products. Because the risk for myopathy is dose-related, Chinese patients should not receive simvastatin 80 mg coadministered with lipid-modifying doses of niacin-containing products. The cause of the increased risk of myopathy is not known. It is also unknown if the risk for myopathy with coadministration of simvastatin with lipid-modifying doses of niacin-containing products observed in Chinese patients applies to other Asian patients. [See Warnings and Precautions (5.1).]

3 DOSAGE FORMS AND STRENGTHS

- Oral Suspension: 20 mg/5 mL (4 mg per mL) off-white to pinkish-orange suspension with a strawberry flavor.
- Oral Suspension: 40 mg/5 mL (8 mg per mL) off-white to pinkish-orange suspension with a strawberry flavor.

4 CONTRAINDICATIONS

FLOLIPID is contraindicated in the following conditions:

- Concomitant administration of strong CYP3A4 inhibitors (e.g., itraconazole, ketoconazole, posaconazole, voriconazole, HIV protease inhibitors, boceprevir, telaprevir, erythromycin, clarithromycin, telithromycin, nefazodone, and cobicistat-containing products) [see Warnings and Precautions (5.1)].
- Concomitant administration of gemfibrozil, cyclosporine, or danazol [see Warnings and Precautions (5.1)].
- Hypersensitivity to any component of this medication [see Adverse Reactions (6.2).]
- Active liver disease, which may include unexplained persistent elevations in hepatic transaminase levels [see Warnings and Precautions (5.3)].
- Women who are pregnant or may become pregnant. Serum cholesterol and triglycerides increase during normal pregnancy, and cholesterol or cholesterol derivatives are essential for fetal development. Because HMG-CoA reductase inhibitors (statins) decrease cholesterol synthesis and possibly the synthesis of other biologically active substances derived from cholesterol, simvastatin may cause fetal harm when administered to a pregnant woman. Atherosclerosis is a chronic process and the discontinuation of lipid-lowering drugs during pregnancy should have little impact on the outcome of long-term therapy of primary hypercholesterolemia. There are no adequate and well-controlled studies of use with simvastatin during pregnancy; however, in rare reports congenital anomalies were observed following intrauterine exposure to statins. In rat and rabbit animal reproduction studies, simvastatin revealed no evidence of teratogenicity. FLOLIPID should be administered to women of childbearing age only when such patients are highly unlikely to conceive. If the patient becomes pregnant while taking this drug, FLOLIPID should be discontinued immediately and the patient should be apprised of the potential hazard to the fetus [see Use in Specific Populations (8.1)] .
- Nursing mothers. It is not known whether simvastatin is excreted into human milk; however, a small amount of another drug in this class does pass into breast milk. Because statins have the potential for serious adverse reactions in nursing infants, women who require treatment with FLOLIPID should not breastfeed their infants [see Use in Specific Populations (8.3)].

5 WARNINGS AND PRECAUTIONS

5.1 Myopathy/Rhabdomyolysis

Simvastatin occasionally causes myopathy manifested as muscle pain, tenderness or weakness with creatine kinase (CK) above ten times the upper limit of normal (ULN). Myopathy sometimes takes the form of rhabdomyolysis with or without acute renal failure secondary to myoglobinuria, and rare fatalities have occurred. The risk of myopathy is increased by high levels of statin activity in plasma. Predisposing factors for myopathy include advanced age (≥65 years), female gender, uncontrolled hypothyroidism, and renal impairment.

The risk of myopathy, including rhabdomyolysis, is dose related. In a clinical trial database in which 41,413 patients were treated with simvastatin, 24,747 (approximately 60%) of whom were enrolled in studies with a median follow-up of at least 4 years, the incidence of myopathy was approximately 0.03% and 0.08% at 20 and 40 mg/day, respectively. The incidence of myopathy with 80 mg (0.61%) was disproportionately higher than that observed at the lower doses. In these trials, patients were carefully monitored and some interacting medicinal products were excluded.

In a clinical trial in which 12,064 patients with a history of myocardial infarction were treated with simvastatin (mean follow-up 6.7 years), the incidence of myopathy (defined as unexplained muscle weakness or pain with a serum creatine kinase [CK] >10 times upper limit of normal [ULN]) in patients on 80 mg/day was approximately 0.9% compared with 0.02% for patients on 20 mg/day. The incidence of rhabdomyolysis (defined as myopathy with a CK >40 times ULN) in patients on 80 mg/day was approximately 0.4% compared with 0% for patients on 20 mg/day. The incidence of myopathy, including rhabdomyolysis, was highest during the first year and then notably decreased during the subsequent years of treatment. In this trial, patients were carefully monitored and some interacting medicinal products were excluded.

The risk of myopathy, including rhabdomyolysis, is greater in patients on simvastatin 80 mg compared with other statin therapies with similar or greater LDL-C-lowering efficacy and compared with lower doses of simvastatin. Therefore, an 80-mg dose of FLOLIPID should be used only in patients who have been taking simvastatin 80 mg chronically (e.g., for 12 months or more) without evidence of muscle toxicity [see Dosage and Administration, Restricted Dosing for 80 mg (2.2)] . If, however, a patient who is currently tolerating the 80-mg dose of FLOLIPID needs to be initiated on an interacting drug that is contraindicated or is associated with a dose cap for simvastatin, that patient should be switched to an alternative statin with less potential for the drug-drug interaction. Patients should be advised of the increased risk of myopathy, including rhabdomyolysis, and to report promptly any unexplained muscle pain, tenderness or weakness. If symptoms occur, treatment should be discontinued immediately. [See Warnings and Precautions (5.2).]

All patients starting therapy with FLOLIPID, or whose dose of FLOLIPID is being increased, should be advised of the risk of myopathy, including rhabdomyolysis, and told to report promptly any unexplained muscle pain, tenderness or weakness particularly if accompanied by malaise or fever or if muscle signs and symptoms persist after discontinuing FLOLIPID. FLOLIPID therapy should be discontinued immediately if myopathy is diagnosed or suspected. In most cases, muscle symptoms and CK increases resolved when treatment was promptly discontinued. Periodic CK determinations may be considered in patients starting therapy with FLOLIPID or whose dose is being increased, but there is no assurance that such monitoring will prevent myopathy.

Many of the patients who have developed rhabdomyolysis on therapy with simvastatin have had complicated medical histories, including renal insufficiency usually as a consequence of long-standing diabetes mellitus. Such patients merit closer monitoring. FLOLIPID therapy should be discontinued if markedly elevated CPK levels occur or myopathy is diagnosed or suspected. FLOLIPID therapy should also be temporarily withheld in any patient experiencing an acute or serious condition predisposing to the development of renal failure secondary to rhabdomyolysis, e.g., sepsis; hypotension; major surgery; trauma; severe metabolic, endocrine, or electrolyte disorders; or uncontrolled epilepsy.

Drug Interactions

The risk of myopathy and rhabdomyolysis is increased by high levels of statin activity in plasma. Simvastatin is metabolized by the cytochrome P450 isoform 3A4. Certain drugs which inhibit this metabolic pathway can raise the plasma levels of simvastatin and may increase the risk of myopathy. These include itraconazole, ketoconazole, posaconazole, voriconazole, the macrolide antibiotics erythromycin and clarithromycin, and the ketolide antibiotic telithromycin, HIV protease inhibitors, boceprevir, telaprevir, the antidepressant nefazodone, cobicistat-containing products, or grapefruit juice [see Clinical Pharmacology (12.3)] . Combination of these drugs with simvastatin is contraindicated. If short-term treatment with strong CYP3A4 inhibitors is unavoidable, therapy with simvastatin must be suspended during the course of treatment. [See Contraindications (4) and Drug Interactions (7.1).]

The combined use of simvastatin with gemfibrozil, cyclosporine, or danazol is contraindicated [see Contraindications (4) and Drug Interactions (7.1 and 7.2)].

Caution should be used when prescribing other fibrates with simvastatin, as these agents can cause myopathy when given alone and the risk is increased when they are co-administered [see Drug Interactions (7.2)] .

Cases of myopathy, including rhabdomyolysis, have been reported with simvastatin coadministered with colchicine, and caution should be exercised when prescribing simvastatin with colchicine [see Drug Interactions (7.7)] .

The benefits of the combined use of simvastatin with the following drugs should be carefully weighed against the potential risks of combinations: other lipid-lowering drugs (other fibrates, ≥1 g/day of niacin, or, for patients with HoFH, lomitapide), amiodarone, dronedarone, verapamil, diltiazem, amlodipine, or ranolazine [see Drug Interactions (7.3) and Table 3 in Clinical Pharmacology (12.3)] [also see Dosage and Administration, Patients with Homozygous Familial Hypercholesterolemia (2.4)] .

Cases of myopathy, including rhabdomyolysis, have been observed with simvastatin coadministered with lipid-modifying doses (≥1 g/day niacin) of niacin-containing products. In an ongoing, double-blind, randomized cardiovascular outcomes trial, an independent safety monitoring committee identified that the incidence of myopathy is higher in Chinese compared with non-Chinese patients taking simvastatin 40 mg coadministered with lipid-modifying doses of a niacin-containing product. Caution should be used when treating Chinese patients with simvastatin in doses exceeding 20 mg/day coadministered with lipid-modifying doses of niacin-containing products. Because the risk for myopathy is dose-related, Chinese patients should not receive simvastatin 80 mg coadministered with lipid-modifying doses of niacin-containing products. It is unknown if the risk for myopathy with coadministration of simvastatin with lipid-modifying doses of niacin-containing products observed in Chinese patients applies to other Asian patients [see Drug Interactions (7.4)] .

Prescribing recommendations for interacting agents are summarized in Table 1 [see also Dosage and Administration (2.3, 2.4), Drug Interactions (7), Clinical Pharmacology (12.3)] .

Table 1:Drug Interactions Associated with Increased Risk of Myopathy/Rhabdomyolysis

Interacting Agents | Prescribing Recommendations
Strong CYP3A4 Inhibitors, e.g.:; Itraconazole; Ketoconazole; Posaconazole; Voriconazole; Erythromycin; Clarithromycin; Telithromycin; HIV protease inhibitors; Boceprevir; Telaprevir; Nefazodone; Cobicistat-containing products; Gemfibrozil; Cyclosporine; Danazol | Contraindicated with simvastatin
Verapamil; Diltiazem; Dronedarone | Do not exceed 10 mg simvastatin daily
Amiodarone; Amlodipine; Ranolazine | Do not exceed 20 mg simvastatin daily
Lomitapide | For patients with HoFH, do not exceed 20 mg simvastatin daily [For patients with HoFH who have been taking 80 mg simvastatin chronically (e.g., for 12 months or more) without evidence of muscle toxicity, do not exceed 40 mg simvastatin when taking lomitapide.]
Grapefruit juice | Avoid grapefruit juice

5.2 Immune-Mediated Necrotizing Myopathy

There have been rare reports of immune-mediated necrotizing myopathy (IMNM), an autoimmune myopathy, associated with statin use. IMNM is characterized by: proximal muscle weakness and elevated serum creatine kinase, which persist despite discontinuation of statin treatment; positive anti-HMG CoA reductase antibody; muscle biopsy showing necrotizing myopathy; and improvement with immunosuppressive agents. Additional neuromuscular and serologic testing may be necessary.

Treatment with immunosuppressive agents may be required. Consider risk of IMNM carefully prior to initiation of a different statin. If therapy is initiated with a different statin, monitor for signs and symptoms of IMNM.

5.3 Liver Dysfunction

Persistent increases (to more than 3X the ULN) in serum transaminases have occurred in approximately 1% of patients who received simvastatin in clinical studies. When drug treatment was interrupted or discontinued in these patients, the transaminase levels usually fell slowly to pretreatment levels. The increases were not associated with jaundice or other clinical signs or symptoms. There was no evidence of hypersensitivity.

In the Scandinavian Simvastatin Survival Study (4S) [see Clinical Studies (14.1)] , the number of patients with more than one transaminase elevation to >3X ULN, over the course of the study, was not significantly different between the simvastatin and placebo groups (14 [0.7%] vs. 12 [0.6%]). Elevated transaminases resulted in the discontinuation of 8 patients from therapy in the simvastatin group (n=2,221) and 5 in the placebo group (n=2,223). Of the 1,986 simvastatin treated patients in 4S with normal liver function tests (LFTs) at baseline, 8 (0.4%) developed consecutive LFT elevations to >3X ULN and/or were discontinued due to transaminase elevations during the 5.4 years (median follow-up) of the study. Among these 8 patients, 5 initially developed these abnormalities within the first year. All of the patients in this study received a starting dose of 20 mg of simvastatin; 37% were titrated to 40 mg.

In 2 controlled clinical studies in 1,105 patients, the 12-month incidence of persistent hepatic transaminase elevation without regard to drug relationship was 0.9% and 2.1% at the 40- and 80-mg dose, respectively. No patients developed persistent liver function abnormalities following the initial 6 months of treatment at a given dose.

It is recommended that liver function tests be performed before the initiation of treatment, and thereafter when clinically indicated. There have been rare postmarketing reports of fatal and non-fatal hepatic failure in patients taking statins, including simvastatin. If serious liver injury with clinical symptoms and/or hyperbilirubinemia or jaundice occurs during treatment with FLOLIPID, promptly interrupt therapy. If an alternate etiology is not found do not restart FLOLIPID. Note that ALT may emanate from muscle, therefore ALT rising with CK may indicate myopathy [see Warnings and Precautions (5.1)] .

The drug should be used with caution in patients who consume substantial quantities of alcohol and/or have a past history of liver disease. Active liver diseases or unexplained transaminase elevations are contraindications to the use of simvastatin.

Moderate (less than 3X ULN) elevations of serum transaminases have been reported following therapy with simvastatin. These changes appeared soon after initiation of therapy with simvastatin, were often transient, were not accompanied by any symptoms and did not require interruption of treatment.

5.4 Endocrine Function

Increases in HbA1c and fasting serum glucose levels have been reported with HMG-CoA reductase inhibitors, including simvastatin.

6 ADVERSE REACTIONS

6.1 Clinical Trials Experience

Because clinical studies are conducted under widely varying conditions, adverse reaction rates observed in the clinical studies of a drug cannot be directly compared to rates in the clinical studies of another drug and may not reflect the rates observed in practice.

In the pre-marketing controlled clinical studies and their open extensions (2,423 patients with median duration of follow-up of approximately 18 months), 1.4% of patients were discontinued due to adverse reactions. The most common adverse reactions that led to treatment discontinuation were: gastrointestinal disorders (0.5%), myalgia (0.1%), and arthralgia (0.1%). The most commonly reported adverse reactions (incidence ≥5%) in simvastatin controlled clinical trials were: upper respiratory infections (9.0%), headache (7.4%), abdominal pain (7.3%), constipation (6.6%), and nausea (5.4%).

Scandinavian Simvastatin Survival Study

In 4S involving 4,444 (age range 35-71 years, 19% women, 100% Caucasians) treated with 20-40 mg/day of simvastatin (n=2,221) or placebo (n=2,223) over a median of 5.4 years, adverse reactions reported in ≥2% of patients and at a rate greater than placebo are shown in Table 2.

Table 2:Adverse Reactions Reported Regardless of Causality by ≥ 2% of Patients Treated with Simvastatin and Greater than Placebo in 4S

 | Simvastatin; (N=2,221); % | Placebo; (N=2,223); %
Body as a Whole
Edema/swelling | 2.7 | 2.3
Abdominal pain | 5.9 | 5.8
Cardiovascular System Disorders
Atrial fibrillation | 5.7 | 5.1
Digestive System Disorders
Constipation | 2.2 | 1.6
Gastritis | 4.9 | 3.9
Endocrine Disorders
Diabetes mellitus | 4.2 | 3.6
Musculoskeletal Disorders
Myalgia | 3.7 | 3.2
Nervous System / Psychiatric Disorders
Headache | 2.5 | 2.1
Insomnia | 4.0 | 3.8
Vertigo | 4.5 | 4.2
Respiratory System Disorders
Bronchitis | 6.6 | 6.3
Sinusitis | 2.3 | 1.8
Skin / Skin Appendage Disorders
Eczema | 4.5 | 3.0
Urogenital System Disorders
Infection, urinary tract | 3.2 | 3.1

Heart Protection Study

In the Heart Protection Study (HPS), involving 20,536 patients (age range 40-80 years, 25% women, 97% Caucasians, 3% other races) treated with simvastatin 40 mg/day (n=10,269) or placebo (n=10,267) over a mean of 5 years, only serious adverse reactions and discontinuations due to any adverse reactions were recorded. Discontinuation rates due to adverse reactions were 4.8% in patients treated with simvastatin compared with 5.1% in patients treated with placebo. The incidence of myopathy/rhabdomyolysis was <0.1% in patients treated with simvastatin.

Other Clinical Studies

In a clinical trial in which 12,064 patients with a history of myocardial infarction were treated with simvastatin (mean follow-up 6.7 years), the incidence of myopathy (defined as unexplained muscle weakness or pain with a serum creatine kinase [CK] >10 times upper limit of normal [ULN]) in patients on 80 mg/day was approximately 0.9% compared with 0.02% for patients on 20 mg/day. The incidence of rhabdomyolysis (defined as myopathy with a CK >40 times ULN) in patients on 80 mg/day was approximately 0.4% compared with 0% for patients on 20 mg/day. The incidence of myopathy, including rhabdomyolysis, was highest during the first year and then notably decreased during the subsequent years of treatment. In this trial, patients were carefully monitored and some interacting medicinal products were excluded.

Other adverse reactions reported in clinical trials were: diarrhea, rash, dyspepsia, flatulence, and asthenia.

Laboratory Tests

Marked persistent increases of hepatic transaminases have been noted [see Warnings and Precautions (5.3)]. Elevated alkaline phosphatase and γ-glutamyl transpeptidase have also been reported. About 5% of patients had elevations of CK levels of 3 or more times the normal value on one or more occasions. This was attributable to the noncardiac fraction of CK. [See Warnings and Precautions (5.1).]

Adolescent Patients (ages 10 to 17 years)

In a 48-week, controlled study in adolescent boys and girls who were at least 1 year post-menarche, 10 to 17 years of age (43.4% female, 97.7% Caucasians, 1.7% Hispanics, 0.6% Multiracial) with heterozygous familial hypercholesterolemia (n=175), treated with placebo or simvastatin (10 to 40 mg daily), the most common adverse reactions observed in both groups were upper respiratory infection, headache, abdominal pain, and nausea [see Use in Specific Populations (8.4) and Clinical Studies (14.2)] .

6.2 Postmarketing Experience

Because the below reactions are reported voluntarily from a population of uncertain size, it is generally not possible to reliably estimate their frequency or establish a causal relationship to drug exposure. The following additional adverse reactions have been identified during postapproval use of simvastatin: pruritus, alopecia, a variety of skin changes (e.g., nodules, discoloration, dryness of skin/mucous membranes, changes to hair/nails), dizziness, muscle cramps, myalgia, pancreatitis, paresthesia, peripheral neuropathy, vomiting, anemia, erectile dysfunction, interstitial lung disease, rhabdomyolysis, hepatitis/jaundice, fatal and non-fatal hepatic failure, and depression.

There have been rare reports of immune-mediated necrotizing myopathy associated with statin use [see Warnings and Precautions (5.1)] .

An apparent hypersensitivity syndrome has been reported rarely which has included some of the following features: anaphylaxis, angioedema, lupus erythematous-like syndrome, polymyalgia rheumatica, dermatomyositis, vasculitis, purpura, thrombocytopenia, leukopenia, hemolytic anemia, positive ANA, ESR increase, eosinophilia, arthritis, arthralgia, urticaria, asthenia, photosensitivity, fever, chills, flushing, malaise, dyspnea, toxic epidermal necrolysis, erythema multiforme, including Stevens-Johnson syndrome.

There have been rare postmarketing reports of cognitive impairment (e.g., memory loss, forgetfulness, amnesia, memory impairment, confusion) associated with statin use. These cognitive issues have been reported for all statins. The reports are generally nonserious, and reversible upon statin discontinuation, with variable times to symptom onset (1 day to years) and symptom resolution (median of 3 weeks).

7 DRUG INTERACTIONS

7.1 Strong CYP3A4 Inhibitors, Cyclosporine, or Danazol

Strong CYP3A4 inhibitors: Simvastatin, like several other inhibitors of HMG-CoA reductase, is a substrate of CYP3A4. Simvastatin is metabolized by CYP3A4 but has no CYP3A4 inhibitory activity; therefore it is not expected to affect the plasma concentrations of other drugs metabolized by CYP3A4.

Elevated plasma levels of HMG-CoA reductase inhibitory activity increases the risk of myopathy and rhabdomyolysis, particularly with higher doses of simvastatin. [See Warnings and Precautions (5.1) and Clinical Pharmacology (12.3).] Concomitant use of drugs labeled as having a strong inhibitory effect on CYP3A4 is contraindicated [see Contraindications (4)]. If treatment with itraconazole, ketoconazole, posaconazole, voriconazole, erythromycin, clarithromycin or telithromycin is unavoidable, therapy with simvastatin must be suspended during the course of treatment.

Cyclosporine or Danazol: The risk of myopathy, including rhabdomyolysis is increased by concomitant administration of cyclosporine or danazol. Therefore, concomitant use of these drugs is contraindicated [see Contraindications (4), Warnings and Precautions (5.1) and Clinical Pharmacology (12.3)] .

7.2 Lipid-Lowering Drugs That Can Cause Myopathy When Given Alone

Gemfibrozil: Contraindicated with simvastatin [see Contraindications (4) and Warnings and Precautions (5.1)].

Other fibrates: Caution should be used when prescribing with simvastatin [see Warnings and Precautions (5.1)].

7.3 Amiodarone, Dronedarone, Ranolazine, or Calcium Channel Blockers

The risk of myopathy, including rhabdomyolysis, is increased by concomitant administration of amiodarone, dronedarone, ranolazine, or calcium channel blockers such as verapamil, diltiazem, or amlodipine [see Dosage and Administration (2.3) and Warnings and Precautions (5.1), and Table 3 in Clinical Pharmacology (12.3)] .

7.4 Niacin

Cases of myopathy/rhabdomyolysis have been observed with simvastatin coadministered with lipid-modifying doses (≥1 g/day niacin) of niacin-containing products. In particular, caution should be used when treating Chinese patients with simvastatin doses exceeding 20 mg/day coadministered with lipid-modifying doses of niacin-containing products. Because the risk for myopathy is dose-related, Chinese patients should not receive simvastatin 80 mg coadministered with lipid-modifying doses of niacin-containing products. [See Warnings and Precautions (5.1) and Clinical Pharmacology (12.3).]

7.5 Digoxin

In one study, concomitant administration of digoxin with simvastatin resulted in a slight elevation in digoxin concentrations in plasma. Patients taking digoxin should be monitored appropriately when simvastatin is initiated [see Clinical Pharmacology (12.3)] .

7.6 Coumarin Anticoagulants

In two clinical studies, one in normal volunteers and the other in hypercholesterolemic patients, simvastatin 20-40 mg/day modestly potentiated the effect of coumarin anticoagulants: the prothrombin time, reported as International Normalized Ratio (INR), increased from a baseline of 1.7 to 1.8 and from 2.6 to 3.4 in the volunteer and patient studies, respectively. With other statins, clinically evident bleeding and/or increased prothrombin time has been reported in a few patients taking coumarin anticoagulants concomitantly. In such patients, prothrombin time should be determined before starting simvastatin and frequently enough during early therapy to ensure that no significant alteration of prothrombin time occurs. Once a stable prothrombin time has been documented, prothrombin times can be monitored at the intervals usually recommended for patients on coumarin anticoagulants. If the dose of simvastatin is changed or discontinued, the same procedure should be repeated. Simvastatin therapy has not been associated with bleeding or with changes in prothrombin time in patients not taking anticoagulants.

7.7 Colchicine

Cases of myopathy, including rhabdomyolysis, have been reported with simvastatin coadministered with colchicine, and caution should be exercised when prescribing simvastatin with colchicine.

8 USE IN SPECIFIC POPULATIONS

8.1 Pregnancy

Pregnancy Category X [See Contraindications (4).]

FLOLIPID is contraindicated in women who are or may become pregnant. Lipid lowering drugs offer no benefit during pregnancy, because cholesterol and cholesterol derivatives are needed for normal fetal development. Atherosclerosis is a chronic process, and discontinuation of lipid-lowering drugs during pregnancy should have little impact on long-term outcomes of primary hypercholesterolemia therapy. There are no adequate and well-controlled studies of use with simvastatin during pregnancy; however, there are rare reports of congenital anomalies in infants exposed to statins in utero. Animal reproduction studies of simvastatin in rats and rabbits showed no evidence of teratogenicity. Serum cholesterol and triglycerides increase during normal pregnancy, and cholesterol or cholesterol derivatives are essential for fetal development. Because statins decrease cholesterol synthesis and possibly the synthesis of other biologically active substances derived from cholesterol, simvastatin may cause fetal harm when administered to a pregnant woman. If FLOLIPID is used during pregnancy or if the patient becomes pregnant while taking this drug, the patient should be apprised of the potential hazard to the fetus.

There are rare reports of congenital anomalies following intrauterine exposure to statins. In a review [Manson, J.M., Freyssinges, C., Ducrocq, M.B., Stephenson, W.P., Postmarketing Surveillance of Lovastatin and Simvastatin Exposure During Pregnancy, Reproductive Toxicology, 10(6): 439-446, 1996.] of approximately 100 prospectively followed pregnancies in women exposed to simvastatin or another structurally related statin, the incidences of congenital anomalies, spontaneous abortions, and fetal deaths/stillbirths did not exceed those expected in the general population. However, the study was only able to exclude a 3- to 4-fold increased risk of congenital anomalies over the background rate. In 89% of these cases, drug treatment was initiated prior to pregnancy and was discontinued during the first trimester when pregnancy was identified.

Simvastatin was not teratogenic in rats or rabbits at doses (25, 10 mg/kg/day, respectively) that resulted in 3 times the human exposure based on mg/m^2 surface area. However, in studies with another structurally-related statin, skeletal malformations were observed in rats and mice.

Women of childbearing potential, who require treatment with FLOLIPID for a lipid disorder, should be advised to use effective contraception. For women trying to conceive, discontinuation of FLOLIPID should be considered. If pregnancy occurs, FLOLIPID should be immediately discontinued.

8.3 Nursing Mothers

It is not known whether simvastatin is excreted in human milk. Because a small amount of another drug in this class is excreted in human milk and because of the potential for serious adverse reactions in nursing infants, women taking simvastatin should not nurse their infants. A decision should be made whether to discontinue nursing or discontinue drug, taking into account the importance of the drug to the mother [see Contraindications (4)].

8.4 Pediatric Use

Safety and effectiveness of simvastatin in patients 10-17 years of age with heterozygous familial hypercholesterolemia have been evaluated in a controlled clinical trial in adolescent boys and in girls who were at least 1 year post-menarche. Patients treated with simvastatin had an adverse reaction profile similar to that of patients treated with placebo. Doses greater than 40 mg have not been studied in this population.. In this limited controlled study, there was no significant effect on growth or sexual maturation in the adolescent boys or girls, or on menstrual cycle length in girls. [See Dosage and Administration (2.5), Adverse Reactions (6.1), Clinical Studies (14.2).] Adolescent females should be counseled on appropriate contraceptive methods while on simvastatin therapy [see Contraindications (4) and Use in Specific Populations (8.1)]. Simvastatin has not been studied in patients younger than 10 years of age, nor in premenarchal girls.

8.5 Geriatric Use

Of the 2,423 patients who received simvastatin in Phase III clinical studies and the 10,269 patients in the Heart Protection Study who received simvastatin, 363 (15%) and 5,366 (52%), respectively were ≥65 years old. In HPS, 615 (6%) were ≥75 years old. No overall differences in safety or effectiveness were observed between these subjects and younger subjects, and other reported clinical experience has not identified differences in responses between the elderly and younger patients, but greater sensitivity of some older individuals cannot be ruled out. Since advanced age (≥65 years) is a predisposing factor for myopathy, FLOLIPID should be prescribed with caution in the elderly. [See Clinical Pharmacology (12.3).]

A pharmacokinetic study with simvastatin showed the mean plasma level of statin activity to be approximately 45% higher in elderly patients between 70 to 78 years of age compared with patients between 18 to 30 years of age. In 4S, 1,021 (23%) of 4,444 patients were 65 or older. Lipid-lowering efficacy was at least as great in elderly patients compared with younger patients, and simvastatin significantly reduced total mortality and CHD mortality in elderly patients with a history of CHD. In HPS, 52% of patients were elderly (4,891 patients 65 to 69 years and 5,806 patients 70 years or older). The relative risk reductions of CHD death, non-fatal MI, coronary and non-coronary revascularization procedures, and stroke were similar in older and younger patients [see Clinical Studies (14.1)]. In HPS, among 32,145 patients entering the active run-in period, there were 2 cases of myopathy/rhabdomyolysis; these patients were aged 67 and 73. Of the 7 cases of myopathy/rhabdomyolysis among 10,269 patients allocated to simvastatin, 4 were aged 65 or more (at baseline), of whom one was over 75. There were no overall differences in safety between older and younger patients in either 4S or HPS.

Because advanced age (≥65 years) is a predisposing factor for myopathy, including rhabdomyolysis, FLOLIPID should be prescribed with caution in the elderly. In a clinical trial of patients treated with simvastatin 80 mg/day, patients ≥65 years of age had an increased risk of myopathy, including rhabdomyolysis, compared to patients <65 years of age. [See Warnings and Precautions (5.1) and Clinical Pharmacology (12.3).]

8.6 Renal Impairment

Caution should be exercised when FLOLIPID is administered to patients with severe renal impairment. [See Dosage and Administration (2.6).]

8.7 Hepatic Impairment

Simvastatin Oral Suspension is contraindicated in patients with active liver disease which may include unexplained persistent elevations in hepatic transaminase levels [see Contraindications (4) and Warnings and Precautions (5.3)] .

10 OVERDOSAGE

Significant lethality was observed in mice after a single oral dose of 9 g/m^2. No evidence of lethality was observed in rats or dogs treated with doses of 30 and 100 g/m^2, respectively. No specific diagnostic signs were observed in rodents. At these doses the only signs seen in dogs were emesis and mucoid stools.

A few cases of overdosage with simvastatin have been reported; the maximum dose taken was 3.6 g. All patients recovered without sequelae. Supportive measures should be taken in the event of an overdose. The dialyzability of simvastatin and its metabolites in man is not known at present.

11 DESCRIPTION

FLOLIPID Oral Suspension is a lipid-lowering agent that is derived synthetically from a fermentation product of Aspergillus terreus.After oral ingestion, simvastatin, which is an inactive lactone, is hydrolyzed to the corresponding β-hydroxyacid form. This is an inhibitor of 3-hydroxy-3-methylglutaryl-coenzyme A (HMG-CoA) reductase. This enzyme catalyzes the conversion of HMG-CoA to mevalonate, which is an early and rate-limiting step in the biosynthesis of cholesterol.

Simvastatin is butanoic acid, 2,2-dimethyl-,1,2,3,7,8,8a-hexahydro-3,7-dimethyl-8-[2-(tetrahydro-4-hydroxy-6-oxo-2 H-pyran-2-yl)-ethyl]-1-naphthalenyl ester, [1 S-[1α,3α,7β,8β(2 S*,4 S*),-8aβ]]. The empirical formula of simvastatin is C25H38O5 and its molecular weight is 418.57. Its structural formula is:

Simvastatin is a white to off-white, nonhygroscopic, crystalline powder that is practically insoluble in water, and freely soluble in chloroform, methanol and ethanol.

FLOLIPID Oral Suspension contains either 20 mg of simvastatin per 5 mL (corresponding to 4 mg per mL) or 40 mg of simvastatin per 5 mL (corresponding to 8 mg per mL) and the following inactive ingredients: acesulfame potassium, carboxymethylcellulose sodium, citric acid monohydrate, ethylparaben, magnesium aluminum silicate, methylparaben, propylene glycol, propylparaben, purified water, simethicone emulsion, sodium lauryl sulfate, sodium phosphate, diabasic, anhydrous, and strawberry flavor.

12 CLINICAL PHARMACOLOGY

12.1 Mechanism of Action

Simvastatin is a prodrug and is hydrolyzed to its active β-hydroxyacid form, simvastatin acid, after administration. Simvastatin is a specific inhibitor of 3-hydroxy-3-methylglutaryl-coenzyme A (HMG-CoA) reductase, the enzyme that catalyzes the conversion of HMG-CoA to mevalonate, an early and rate limiting step in the biosynthetic pathway for cholesterol. In addition, simvastatin reduces VLDL and TG and increases HDL-C.

12.2 Pharmacodynamics

Epidemiological studies have demonstrated that elevated levels of total-C, LDL-C, as well as decreased levels of HDL-C are associated with the development of atherosclerosis and increased cardiovascular risk. Lowering LDL-C decreases this risk. However, the independent effect of raising HDL-C or lowering TG on the risk of coronary and cardiovascular morbidity and mortality has not been determined.

12.3 Pharmacokinetics

Simvastatin is a lactone that is readily hydrolyzed in vivo to the corresponding β-hydroxyacid, a potent inhibitor of HMG-CoA reductase. Inhibition of HMG-CoA reductase is the basis for an assay in pharmacokinetic studies of the β-hydroxyacid metabolites (active inhibitors) and, following base hydrolysis, active plus latent inhibitors (total inhibitors) in plasma following administration of simvastatin.

In a food effect study for simvastatin oral suspension, subjects who ate a high fat meal (about 540 calories and 56% fat) demonstrated an 18% decrease in simvastatin AUC0-∞ and a 44% increase in ß-hydroxyacid simvastatin AUC0-∞, compared with what was observed in the fasted state.

Following an oral dose of^14C-labeled simvastatin in man, 13% of the dose was excreted in urine and 60% in feces. Plasma concentrations of total radioactivity (simvastatin plus^14C-metabolites) peaked at 4 hours and declined rapidly to about 10% of peak by 12 hours postdose. Since simvastatin undergoes extensive first-pass extraction in the liver, the availability of the drug to the general circulation is low (<5%).

Both simvastatin and its β-hydroxyacid metabolite are highly bound (approximately 95%) to human plasma proteins. Rat studies indicate that when radiolabeled simvastatin was administered, simvastatin -derived radioactivity crossed the blood-brain barrier.

The major active metabolites of simvastatin present in human plasma are the β-hydroxyacid of simvastatin and its 6′-hydroxy, 6′-hydroxymethyl, and 6′-exomethylene derivatives. Peak plasma concentrations of both active and total inhibitors were attained within 1.3 to 2.4 hours postdose. While the recommended therapeutic dose range is 5 to 40 mg/day, there was no substantial deviation from linearity of AUC of inhibitors in the general circulation with an increase in dose to as high as 120 mg. Relative to the fasting state, the plasma profile of inhibitors was not affected when simvastatin was administered immediately before an American Heart Association recommended low-fat meal.

In a study including 16 elderly patients between 70 and 78 years of age who received simvastatin 40 mg/day, the mean plasma level of HMG-CoA reductase inhibitory activity was increased approximately 45% compared with 18 patients between 18-30 years of age. Clinical study experience in the elderly (n=1522), suggests that there were no overall differences in safety between elderly and younger patients [see Use in Specific Populations (8.5)].

Kinetic studies with another statin, having a similar principal route of elimination, have suggested that for a given dose level higher systemic exposure may be achieved in patients with severe renal insufficiency (as measured by creatinine clearance).

Simvastatin acid is a substrate of the transport protein OATP1B1. Concomitant administration of medicinal products that are inhibitors of the transport protein OATP1B1 may lead to increased plasma concentrations of simvastatin acid and an increased risk of myopathy. For example, cyclosporine has been shown to increase the AUC of statins; although the mechanism is not fully understood, the increase in AUC for simvastatin acid is presumably due, in part, to inhibition of CYP3A4 and/or OATP1B1.

The risk of myopathy is increased by high levels of HMG-CoA reductase inhibitory activity in plasma. Inhibitors of CYP3A4 can raise the plasma levels of HMG-CoA reductase inhibitory activity and increase the risk of myopathy [see Warnings and Precautions (5.1) and Drug Interactions (7.1)] .

Table 3: Effect of Coadministered Drugs or Grapefruit Juice on Simvastatin Systemic Exposure

Coadministered Drug or Grapefruit Juice | Dosing of Coadministered Drug or Grapefruit Juice |  |  | Dosing of Simvastatin | geometric mean ratio (ratio [Results based on a chemical assay except results with propranolol as indicated.] with / without coadministered drug) no effect = 1.00
Coadministered Drug or Grapefruit Juice |  |  |  | Dosing of Simvastatin |  | AUC | Cmax
Contraindicated with simvastatin [see Contraindications (4) and Warnings and Precautions (5.1)]
Telithromycin | 200 mg QD for 4 days |  |  | 80 mg | simvastatin acid [Results could be representative of the following CYP3A4 inhibitors: ketoconazole, erythromycin, clarithromycin, HIV protease inhibitors, and nefazodone.] simvastatin | 12 8.9 | 15 5.3
Nelfinavir [Simvastatin acid refers to the β-hydroxyacid of simvastatin.] | 1250 mg BID for 14 days |  |  | 20 mg QD for 28 days | simvastatin acid simvastatin | 6 | 6.2
Itraconazole | 200 mg QD for 4 days |  |  | 80 mg | simvastatin acid simvastatin |  | 13.1; 13.1
Posaconazole | 100 mg (oral suspension); QD for 13 days; 200 mg (oral suspension); QD for 13 days |  |  | 40 mg; 40 mg | simvastatin acid simvastatin; simvastatin acid simvastatin | 7.3; 10.3; 8.5; 10.6 | 9.2; 9.4; 9.5; 11.4
Gemfibrozil | 600 mg BID for 3 days |  |  | 40 mg | simvastatin acid simvastatin | 2.85; 1.35 | 2.18; 0.91
Avoid grapefruit juice with simvastatin [see Warnings and Precautions (5.1)]
Grapefruit Juice [The effect of amounts of grapefruit juice between those used in these two studies on simvastatin pharmacokinetics has not been studied.]; (high dose) | 200 mL of double-strength TID [Double-strength: one can of frozen concentrate diluted with one can of water. Grapefruit juice was administered TID for 2 days, and 200 mL together with single dose simvastatin and 30 and 90 minutes following single dose simvastatin on Day 3.] |  |  | 60 mg single dose | simvastatin acid simvastatin | 7 16
Grapefruit Juice; (low dose) | 8 oz (about 237mL) of single-strength [Single-strength: one can of frozen concentrate diluted with 3 cans of water. Grapefruit juice was administered with breakfast for 3 days, and simvastatin was administered in the evening on Day 3.] |  |  | 20 mg single dose | simvastatin acid simvastatin | 1.3 1.9
Avoid taking with >10 mg simvastatin, based on clinical and/or post-marketing experience [see Warnings and Precautions (5.1)]
Verapamil SR | 240 mg QD Days 1-7 then 240 mg BID on Days 8-10 |  |  | 80 mg on Day 10 | simvastatin acid simvastatin | 2.3 2.5 | 2.4 2.1
Diltiazem | - 120 mg BID for 10 days |  |  | 80 mg on Day 10 | simvastatin acid; simvastatin | 2.69; 3.10 | 2.69; 2.88
Diltiazem | - 120 mg BID for 14 days |  |  | 20 mg on Day 14 | simvastatin | 4.6 | 3.6
Dronedarone | 400 mg BID for 14 days |  |  | 40 mg QD for 14 days | simvastatin acid simvastatin | 1.96 3.90 | 2.14 3.75
Avoid taking with >20 mg simvastatin, based on clinical and/or post-marketing experience [see Warnings and Precautions (5.1)]
Amiodarone | 400 mg QD for 3 days | 40 mg on Day 3 |  |  | simvastatin acid simvastatin | 1.75 1.76 | 1.72 1.79
Amlodipine | 10 mg QD x 10 days | 80 mg on Day 10 |  |  | simvastatin acid simvastatin | 1.58; 1.77 | 1.56; 1.47
Ranolazine SR | 1000 mg BID for 7 days | 80 mg on Day 1 and Days 6-9 |  |  | simvastatin acid; simvastatin | 2.26; 1.86 | 2.28; 1.75
Avoid taking with >20 mg simvastatin (or 40 mg for patients who have previously taken 80 mg simvastatin chronically, e.g., for 12 months or more, without evidence of muscle toxicity), based on clinical experience
Lomitapide | 60 mg QD for 7 days | 40 mg single dose |  |  | simvastatin acid; simvastatin | 1.7; 2 | 1.6; 2
Lomitapide | 10 mg QD for 7 days | 20 mg single dose |  |  | simvastatin acid; simvastatin | 1.4; 1.6 | 1.4; 1.7
No dosing adjustments required for the following:
Fenofibrate | 160 mg QD X 14 days |  | 80 mg QD on Days 8-14 |  | simvastatin acid simvastatin | 0.64 0.89 | 0.89 0.83
Niacin extended-release [Because Chinese patients have an increased risk for myopathy with simvastatin coadministered with lipid-modifying doses (≥ 1 gram/day niacin) of niacin-containing products, and the risk is dose-related, Chinese patients should not receive simvastatin 80 mg coadministered with lipid-modifying doses of niacin-containing products [see Warnings and Precautions (5.1) and Drug Interactions (7.4)] .] | 2 g single dose |  | 20 mg single dose |  | simvastatin acid simvastatin | 1.6 1.4 | 1.84 1.08
Propranolol | 80 mg single dose |  | 80 mg single dose |  | total inhibitor; active inhibitor | 0.79; 0.79 | ↓ from 33.6 to 21.1 ng∙eq/mL ↓ from 7.0 to 4.7 ng∙eq/mL

In a study of 12 healthy volunteers, simvastatin at the 80-mg dose had no effect on the metabolism of the probe cytochrome P450 isoform 3A4 (CYP3A4) substrates midazolam and erythromycin. This indicates that simvastatin is not an inhibitor of CYP3A4, and, therefore, is not expected to affect the plasma levels of other drugs metabolized by CYP3A4.

Coadministration of simvastatin (40 mg QD for 10 days) resulted in an increase in the maximum mean levels of cardioactive digoxin (given as a single 0.4 mg dose on day 10) by approximately 0.3 ng/mL.

13 NONCLINICAL TOXICOLOGY

13.1 Carcinogenesis, Mutagenesis, Impairment of Fertility

In a 72-week carcinogenicity study, mice were administered daily doses of simvastatin of 25, 100, and 400 mg/kg body weight, which resulted in mean plasma drug levels approximately 1, 4, and 8 times higher than the mean human plasma drug level, respectively (as total inhibitory activity based on AUC) after an 80-mg oral dose. Liver carcinomas were significantly increased in high-dose females and mid- and high-dose males with a maximum incidence of 90% in males. The incidence of adenomas of the liver was significantly increased in mid- and high-dose females. Drug treatment also significantly increased the incidence of lung adenomas in mid- and high-dose males and females. Adenomas of the Harderian gland (a gland of the eye of rodents) were significantly higher in high-dose mice than in controls. No evidence of a tumorigenic effect was observed at 25 mg/kg/day.

In a separate 92-week carcinogenicity study in mice at doses up to 25 mg/kg/day, no evidence of a tumorigenic effect was observed (mean plasma drug levels were 1 times higher than humans given 80 mg simvastatin as measured by AUC).

In a two-year study in rats at 25 mg/kg/day, there was a statistically significant increase in the incidence of thyroid follicular adenomas in female rats exposed to approximately 11 times higher levels of simvastatin than in humans given 80 mg simvastatin (as measured by AUC).

A second two-year rat carcinogenicity study with doses of 50 and 100 mg/kg/day produced hepatocellular adenomas and carcinomas (in female rats at both doses and in males at 100 mg/kg/day). Thyroid follicular cell adenomas were increased in males and females at both doses; thyroid follicular cell carcinomas were increased in females at 100 mg/kg/day. The increased incidence of thyroid neoplasms appears to be consistent with findings from other statins. These treatment levels represented plasma drug levels (AUC) of approximately 7 and 15 times (males) and 22 and 25 times (females) the mean human plasma drug exposure after an 80 milligram daily dose.

No evidence of mutagenicity was observed in a microbial mutagenicity (Ames) test with or without rat or mouse liver metabolic activation. In addition, no evidence of damage to genetic material was noted in an in vitro alkaline elution assay using rat hepatocytes, a V-79 mammalian cell forward mutation study, an in vitro chromosome aberration study in CHO cells, or an in vivo chromosomal aberration assay in mouse bone marrow.

There was decreased fertility in male rats treated with simvastatin for 34 weeks at 25 mg/kg body weight (4 times the maximum human exposure level, based on AUC, in patients receiving 80 mg/day); however, this effect was not observed during a subsequent fertility study in which simvastatin was administered at this same dose level to male rats for 11 weeks (the entire cycle of spermatogenesis including epididymal maturation). No microscopic changes were observed in the testes of rats from either study. At 180 mg/kg/day, (which produces exposure levels 22 times higher than those in humans taking 80 mg/day based on surface area, mg/m^2), seminiferous tubule degeneration (necrosis and loss of spermatogenic epithelium) was observed. In dogs, there was drug-related testicular atrophy, decreased spermatogenesis, spermatocytic degeneration and giant cell formation at 10 mg/kg/day, (approximately 2 times the human exposure, based on AUC, at 80 mg/day). The clinical significance of these findings is unclear.

13.2 Animal Toxicology and/or Pharmacology

CNS Toxicity

Optic nerve degeneration was seen in clinically normal dogs treated with simvastatin for 14 weeks at 180 mg/kg/day, a dose that produced mean plasma drug levels about 12 times higher than the mean plasma drug level in humans taking 80 mg/day.

A chemically similar drug in this class also produced optic nerve degeneration (Wallerian degeneration of retinogeniculate fibers) in clinically normal dogs in a dose-dependent fashion starting at 60 mg/kg/day, a dose that produced mean plasma drug levels about 30 times higher than the mean plasma drug level in humans taking the highest recommended dose (as measured by total enzyme inhibitory activity). This same drug also produced vestibulocochlear Wallerian-like degeneration and retinal ganglion cell chromatolysis in dogs treated for 14 weeks at 180 mg/kg/day, a dose that resulted in a mean plasma drug level similar to that seen with the 60 mg/kg/day dose.

CNS vascular lesions, characterized by perivascular hemorrhage and edema, mononuclear cell infiltration of perivascular spaces, perivascular fibrin deposits and necrosis of small vessels were seen in dogs treated with simvastatin at a dose of 360 mg/kg/day, a dose that produced mean plasma drug levels that were about 14 times higher than the mean plasma drug levels in humans taking 80 mg/day. Similar CNS vascular lesions have been observed with several other drugs of this class.

There were cataracts in female rats after two years of treatment with 50 and 100 mg/kg/day (22 and 25 times the human AUC at 80 mg/day, respectively) and in dogs after three months at 90 mg/kg/day (19 times) and at two years at 50 mg/kg/day (5 times).

14 CLINICAL STUDIES

14.1 Clinical Studies in Adults

Reductions in Risk of CHD Mortality and Cardiovascular Events

In 4S, the effect of therapy with simvastatin on total mortality was assessed in 4,444 patients with CHD and baseline total cholesterol 212-309 mg/dL (5.5 to 8.0 mmol/L). In this multicenter, randomized, double-blind, placebo-controlled study, patients were treated with standard care, including diet, and either simvastatin 20 to 40 mg/day (n=2,221) or placebo (n=2,223) for a median duration of 5.4 years. Over the course of the study, treatment with simvastatin led to mean reductions in total-C, LDL-C and TG of 25%, 35%, and 10%, respectively, and a mean increase in HDL-C of 8%. Simvastatin significantly reduced the risk of mortality by 30% (p=0.0003, 182 deaths in the simvastatin group vs 256 deaths in the placebo group). The risk of CHD mortality was significantly reduced by 42% (p=0.00001, 111 vs 189 deaths). There was no statistically significant difference between groups in non-cardiovascular mortality. Simvastatin significantly decreased the risk of having major coronary events (CHD mortality plus hospital-verified and silent non-fatal myocardial infarction [MI]) by 34% (p<0.00001, 431 vs 622 patients with one or more events). The risk of having a hospital-verified non-fatal MI was reduced by 37%. Simvastatin significantly reduced the risk for undergoing myocardial revascularization procedures (coronary artery bypass grafting or percutaneous transluminal coronary angioplasty) by 37% (p<0.00001, 252 vs 383 patients). Simvastatin significantly reduced the risk of fatal plus non-fatal cerebrovascular events (combined stroke and transient ischemic attacks) by 28% (p=0.033, 75 vs 102 patients). Simvastatin reduced the risk of major coronary events to a similar extent across the range of baseline total and LDL cholesterol levels. Because there were only 53 female deaths, the effect of simvastatin on mortality in women could not be adequately assessed. However, simvastatin significantly lessened the risk of having major coronary events by 34% (60 vs 91 women with one or more event). The randomization was stratified by angina alone (21% of each treatment group) or a previous MI. Because there were only 57 deaths among the patients with angina alone at baseline, the effect of simvastatin on mortality in this subgroup could not be adequately assessed. However, trends in reduced coronary mortality, major coronary events and revascularization procedures were consistent between this group and the total study cohort. Additionally, simvastatin resulted in similar decreases in relative risk for total mortality, CHD mortality, and major coronary events in elderly patients (≥65 years), compared with younger patients.

The Heart Protection Study (HPS) was a large, multi-center, placebo-controlled, double-blind study with a mean duration of 5 years conducted in 20,536 patients (10,269 on simvastatin 40 mg and 10,267 on placebo). Patients were allocated to treatment using a covariate adaptive method^3 which took into account the distribution of 10 important baseline characteristics of patients already enrolled and minimized the imbalance of those characteristics across the groups. Patients had a mean age of 64 years (range 40 to 80 years), were 97% Caucasian and were at high risk of developing a major coronary event because of existing CHD (65%), diabetes (Type 2, 26%; Type 1, 3%), history of stroke or other cerebrovascular disease (16%), peripheral vessel disease (33%), or hypertension in males ≥65 years (6%). At baseline, 3,421 patients (17%) had LDL-C levels below 100 mg/dL, of whom 953 (5%) had LDL-C levels below 80 mg/dL; 7,068 patients (34%) had levels between 100 and 130 mg/dL; and 10,047 patients (49%) had levels greater than 130 mg/dL.

The HPS results showed that simvastatin 40 mg/day significantly reduced: total and CHD mortality; non-fatal MI, stroke, and revascularization procedures (coronary and non-coronary) (see Table 4).

^3D.R. Taves, Minimization: a new method of assigning patients to treatment and control groups. Clin. Pharmacol. Ther. 15 (1974), pp. 443-453

Table 4:Summary of Heart Protection Study Results

Endpoint | Simvastatin; (N=10,269); n (%) [n = number of patients with indicated event] | Placebo; (N=10,267); n (%) | Risk Reduction (%) (95% CI) | p-Value
Primary
- Mortality | 1,328 (12.9) | 1,507 (14.7) | 13 (6 - 19) | p=0.0003
- CHD mortality | 587 (5.7) | 707 (6.9) | 18 (8 - 26) | p=0.0005
Secondary
- Non-fatal MI | 357 (3.5) | 574 (5.6) | 38 (30 - 46) | p<0.0001
- Stroke | 444 (4.3) | 585 (5.7) | 25 (15 - 34) | p<0.0001
Tertiary
- Coronary revascularization | 513 (5) | 725 (7.1) | 30 (22 - 38) | p<0.0001
- Peripheral and other non-coronary revascularization | 450 (4.4) | 532 (5.2) | 16 (5 - 26) | p=0.006

Two composite endpoints were defined in order to have sufficient events to assess relative risk reductions across a range of baseline characteristics (see Figure 1). A composite of major coronary events (MCE) was comprised of CHD mortality and non-fatal MI (analyzed by time-to-first event; 898 patients treated with simvastatin had events and 1,212 patients on placebo had events). A composite of major vascular events (MVE) was comprised of MCE, stroke and revascularization procedures including coronary, peripheral and other non-coronary procedures (analyzed by time-to-first event; 2,033 patients treated with simvastatin had events and 2,585 patients on placebo had events). Significant relative risk reductions were observed for both composite endpoints (27% for MCE and 24% for MVE, p<0.0001). Treatment with simvastatin produced significant relative risk reductions for all components of the composite endpoints. The risk reductions produced by simvastatin in both MCE and MVE were evident and consistent regardless of cardiovascular disease related medical history at study entry (i.e., CHD alone; or peripheral vascular disease, cerebrovascular disease, diabetes or treated hypertension, with or without CHD), gender, age, creatinine levels up to the entry limit of 2.3 mg/dL, baseline levels of LDL-C, HDL-C, apolipoprotein B and A-1, baseline concomitant cardiovascular medications (i.e., aspirin, beta blockers, or calcium channel blockers), smoking status, alcohol intake, or obesity. Diabetics showed risk reductions for MCE and MVE due to simvastatin treatment regardless of baseline HbA1c levels or obesity with the greatest effects seen for diabetics without CHD.

Figure 1 The Effects of Treatment with Simvastatin on Major Vascular Events and Major Coronary Events in HPS

N = number of patients in each subgroup. The inverted triangles are point estimates of the relative risk, with their 95% confidence intervals represented as a line. The area of a triangle is proportional to the number of patients with MVE or MCE in the subgroup relative to the number with MVE or MCE, respectively, in the entire study population. The vertical solid line represents a relative risk of one. The vertical dashed line represents the point estimate of relative risk in the entire study population.

Angiographic Studies

In the Multicenter Anti-Atheroma Study, the effect of simvastatin on atherosclerosis was assessed by quantitative coronary angiography in hypercholesterolemic patients with CHD. In this randomized, double-blind, controlled study, patients were treated with simvastatin 20 mg/day or placebo. Angiograms were evaluated at baseline, two and four years. The co-primary study endpoints were mean change per-patient in minimum and mean lumen diameters, indicating focal and diffuse disease, respectively. Simvastatin significantly slowed the progression of lesions as measured in the Year 4 angiogram by both parameters, as well as by change in percent diameter stenosis. In addition, simvastatin significantly decreased the proportion of patients with new lesions and with new total occlusions.

Modifications of Lipid Profiles

Primary Hyperlipidemia (Fredrickson type IIa and IIb)

Simvastatin has been shown to be effective in reducing total-C and LDL-C in heterozygous familial and non-familial forms of hyperlipidemia and in mixed hyperlipidemia. Maximal to near maximal response is generally achieved within 4 to 6 weeks and maintained during chronic therapy. Simvastatin significantly decreased total-C, LDL-C, total-C/HDL-C ratio, and LDL-C/HDL-C ratio; simvastatin also decreased TG and increased HDL-C (see Table 5).

Table 5:Mean Response in Patients with Primary Hyperlipidemia and Combined (mixed) Hyperlipidemia (Mean Percent Change from Baseline After 6 to 24 Weeks)

- TREATMENT | - N | TOTAL-C | LDL-C | HDL-C | TG*
Lower Dose Comparative Study†
- (Mean % Change at Week 6)
- Simvastatin 5 mg q.p.m. | - 109 | -19 | -26 | 10 | -12
- Simvastatin 10 mg q.p.m. | - 110 | -23 | -30 | 12 | -15
Scandinavian Simvastatin Survival Study‡ (Mean % Change at Week 6)
- Placebo | - 2223 | -1 | -1 | 0 | -2
- Simvastatin 20 mg q.p.m. | - 2221 | -28 | -38 | 8 | -19
- Upper Dose Comparative Study§
- (Mean % Change Averaged at Weeks 18 and 24)
- Simvastatin 40 mg q.p.m. | - 433 | -31 | -41 | 9 | -18
- Simvastatin 80 mg q.p.m.¶ | - 664 | -36 | -47 | 8 | -24
- Multi-Center Combined Hyperlipidemia Study# (Mean % Change at Week 6)
- Placebo | - 125 | 1 | 2 | 3 | -4
- Simvastatin 40 mg q.p.m. | - 123 | -25 | -29 | 13 | -28
- Simvastatin 80 mg q.p.m. | - 124 | -31 | -36 | 16 | -33

* median percent change
† mean baseline LDL-C 244 mg/dL and median baseline TG 168 mg/dL
‡ mean baseline LDL-C 188 mg/dL and median baseline TG 128 mg/dL
§ mean baseline LDL-C 226 mg/dL and median baseline TG 156 mg/dL
¶ 21% and 36% median reduction in TG in patients with TG ≤200 mg/dL and TG >200 mg/dL, respectively. Patients with TG >350 mg/dL were excluded
# mean baseline LDL-C 156 mg/dL and median baseline TG 391 mg/dL

Hypertriglyceridemia (Fredrickson type IV)

The results of a subgroup analysis in 74 patients with type IV hyperlipidemia from a 130-patient, double-blind, placebo-controlled, 3-period crossover study are presented in Table 6.

Table 6:Six-week, Lipid-lowering Effects of Simvastatin in Type IV Hyperlipidemia Median Percent Change (25th and 75th percentile) from Baseline*

- TREATMENT | N | Total-C | LDL-C | HDL-C | TG | VLDL-C | Non-; HDL-C
- Placebo | 74 | +2 | +1 | +3 | -9 | -7 | +1
 |  | (-7, +7) | (-8, +14) | (-3, +10) | (-25, +13) | (-25, +11) | (-9, +8)
- Simvastatin 40 mg/day | 74 | -25 | -28 | +11 | -29 | -37 | -32
 |  | (-34, -19) | (-40, -17) | (+5, +23) | (-43, -16) | (-54, -23) | (-42, -23)
- Simvastatin 80 mg/day | 74 | -32 | -37 | +15 | -34 | -41 | -38
 |  | (-38, -24) | (-46, -26) | (+5, +23) | (-45, -18) | (-57, -28) | (-49, -32)

*The median baseline values (mg/dL) for the patients in this study were: total-C = 254, LDL-C = 135, HDL-C = 36, TG = 404, VLDL-C = 83, and non-HDL-C = 215.

Dysbetalipoproteinemia (Fredrickson type III)

The results of a subgroup analysis in 7 patients with type lll hyperlipidemia (dysbetalipoproteinemia) (apo E2/2) (VLDL-C/TG>0.25) from a 130-patient, double-blind, placebo-controlled, 3-period crossover study are presented in Table 7.

- Table 7:Six-week, Lipid-lowering Effects of Simvastatin in Type III Hyperlipidemia Median Percent Change (min, max) from Baseline [The median baseline values (mg/dL) were: total-C=324, LDL-C=121, HDL-C=31, TG=411, VLDL-C=170, and non-HDL-C = 291.]
- TREATMENT | N | Total-C | LDL-C + IDL | HDL-C | TG | VLDL-C + IDL | Non-HDL-C
- Placebo | 7 | -8 | -8 | -2 | +4 | -4 | -8
 |  | (-24, +34) | (-27, +23) | (-21, +16) | (-22, +90) | (-28, +78) | (-26, -39)
- Simvastatin 40 mg/day | 7 | -50 | -50 | +7 | -41 | -58 | -57
 |  | (-66, -39) | (-60, -31) | (-8, +23) | (-74, -16) | (-90, -37) | (-72, -44)
- Simvastatin 80 mg/day | 7 | -52 | -51 | +7 | -38 | -60 | -59
 |  | (-55, -41) | (-57, -28) | (-5, +59) | (-58, +2) | (-72, -39) | (-61, -46)

Homozygous Familial Hypercholesterolemia

In a controlled clinical study, 12 patients 15 to 39 years of age with homozygous familial hypercholesterolemia received simvastatin 40 mg/day in a single dose or in 3 divided doses, or 80 mg/day in 3 divided doses. In 11 patients with reductions in LDL-C, the mean LDL-C changes for the 40- and 80-mg doses were 14% (range 8% to 23%, median 12%) and 30% (range 14% to 46%, median 29%), respectively. One patient had an increase of 15% in LDL-C. Another patient with absent LDL-C receptor function had an LDL-C reduction of 41% with the 80-mg dose.

Endocrine Function

In clinical studies, simvastatin did not impair adrenal reserve or significantly reduce basal plasma cortisol concentration. Small reductions from baseline in basal plasma testosterone in men were observed in clinical studies with simvastatin, an effect also observed with other statins and the bile acid sequestrant cholestyramine. There was no effect on plasma gonadotropin levels. In a placebo-controlled, 12-week study there was no significant effect of simvastatin 80 mg on the plasma testosterone response to human chorionic gonadotropin. In another 24-week study, simvastatin 20 to 40 mg had no detectable effect on spermatogenesis. In 4S, in which 4,444 patients were randomized to simvastatin 20 to 40 mg/day or placebo for a median duration of 5.4 years, the incidence of male sexual adverse events in the two treatment groups was not significantly different. Because of these factors, the small changes in plasma testosterone are unlikely to be clinically significant. The effects, if any, on the pituitary-gonadal axis in pre-menopausal women are unknown.

14.2 Clinical Studies in Adolescents

In a double-blind, placebo-controlled study, 175 patients (99 adolescent boys and 76 post-menarchal girls) 10-17 years of age (mean age 14.1 years) with heterozygous familial hypercholesterolemia (HeFH) were randomized to simvastatin (n=106) or placebo (n=67) for 24 weeks (base study). Inclusion in the study required a baseline LDL-C level between 160 and 400 mg/dL and at least one parent with an LDL-C level >189 mg/dL. The dosage of simvastatin (once daily in the evening) was 10 mg for the first 8 weeks, 20 mg for the second 8 weeks, and 40 mg thereafter. In a 24-week extension, 144 patients elected to continue therapy with simvastatin 40 mg or placebo.

Simvastatin significantly decreased plasma levels of total-C, LDL-C, and Apo B (see Table 8). Results from the extension at 48 weeks were comparable to those observed in the base study.

Table 8: Lipid-Lowering Effects of Simvastatin in Adolescent Patients with Heterozygous Familial Hypercholesterolemia (Mean Percent Change from Baseline)

Dosage | Duration | N |  | Total-C | LDL-C | HDL-C | TG* | Apo B
Placebo | 24 Weeks | 67 | % Change from Baseline (95% CI) | 1.6 (-2.2, 5.3) | 1.1 (-3.4, 5.5) | 3.6 (-0.7, 8.0) | -3.2 (-11.8, 5.4) | -0.5 (-4.7, 3.6)
 |  |  | Mean baseline, mg/dL (SD) | 278.6; (51.8) | 211.9; (49.0) | 46.9; (11.9) | 90.0; (50.7) | 186.3; (38.1)
Simvastatin | 24 Weeks | 106 | % Change from Baseline (95% CI) | -26.5; (-29.6, -23.3) | -36.8; (-40.5, -33.0) | 8.3; (4.6, 11.9) | -7.9; (-15.8, 0.0) | -32.4; (-35.9, -29.0)
 |  |  | Mean baseline, mg/dL; (SD) | 270.2; (44.0) | 203.8; (41.5) | 47.7; (9.0) | 78.3; (46.0) | 179.9; (33.8)

*median percent change

After 24 weeks of treatment, the mean achieved LDL-C value was 124.9 mg/dL (range: 64.0 to 289.0 mg/dL) in the simvastatin 40 mg group compared to 207.8 mg/dL (range: 128.0 to 334.0 mg/dL) in the placebo group.

The safety and efficacy of doses above 40 mg daily have not been studied in children with HeFH. The long-term efficacy of simvastatin therapy in childhood to reduce morbidity and mortality in adulthood has not been established.

16 HOW SUPPLIED/STORAGE AND HANDLING

FLOLIPID (simvastatin) Oral Suspension 20 mg/5 mL (4 mg per mL) is an off white to pinkish orange suspension with a strawberry flavor. It is supplied as follows:
NDC 29273-401-04 – 150 mL amber glass bottle with a white HDPE Child Resistant Closure

FLOLIPID (simvastatin) Oral Suspension 40 mg/5 mL (8 mg per mL) is an off white to pinkish orange suspension with a strawberry flavor. It is supplied as follows:
NDC 29273-402-04 – 150 mL amber glass bottle with a white HDPE Child Resistant Closure

Storage

Store at 20°-25°C (68°-77°F) [see USP Controlled Room Temperature].
Protect from heat.
Do not freeze or refrigerate.
Use within 30 days after opening

17 PATIENT COUNSELING INFORMATION

Patients should be advised to adhere to their National Cholesterol Education Program (NCEP)-recommended diet, a regular exercise program, and periodic testing of a fasting lipid panel.

Patients should be advised about substances they should not take concomitantly with simvastatin [ see Contraindications (4) and Warnings and Precautions (5.1)]. Patients should also be advised to inform other healthcare professionals prescribing a new medication or increasing the dose of an existing medication that they are taking FLOLIPID.

Muscle Pain

All patients starting therapy with FLOLIPID should be advised of the risk of myopathy, including rhabdomyolysis, and told to report promptly any unexplained muscle pain, tenderness or weakness particularly if accompanied by malaise or fever or if these muscle signs or symptoms persist after discontinuing FLOLIPID. Patients using an 80-mg dose should be informed that the risk of myopathy, including rhabdomyolysis, is increased with use of an 80-mg dose. The risk of myopathy, including rhabdomyolysis, occurring with use of FLOLIPID is increased when taking certain types of medication or consuming grapefruit juice. Patients should discuss all medication, both prescription and over the counter, with their healthcare professional.

Liver Enzymes

It is recommended that liver function tests be performed before the initiation of FLOLIPID, and thereafter when clinically indicated. All patients treated with FLOLIPID should be advised to report promptly any symptoms that may indicate liver injury, including fatigue, anorexia, right upper abdominal discomfort, dark urine or jaundice.

Administration

Instruct patients to take FLOLIPID in the evening on an empty stomach and to shake bottle well for at least 20 seconds before using. Advise patients to measure FLOLIPID with an accurate measuring device. A household teaspoon is not an accurate measuring device and could lead to overdosage. Instruct patients to ask their pharmacist to recommend an appropriate measuring device and to provide instructions for measuring the correct dose.

Pregnancy

Women of childbearing age should be advised to use an effective method of birth control to prevent pregnancy while using FLOLIPID. Discuss future pregnancy plans with your patients, and discuss when to stop taking FLOLIPID if they are trying to conceive. Patients should be advised that if they become pregnant they should stop taking FLOLIPID and call their healthcare professional.

Breastfeeding

Women who are breastfeeding should not use FLOLIPID. Patients who have a lipid disorder and are breastfeeding should be advised to discuss the options with their healthcare professional.

Made in United Kingdom
Manufactured By:
Rosemont Pharmaceuticals Ltd.
United Kingdom (GBN)
Manufactured For
Salerno Pharmaceuticals LP
Brooksville, FL 34604

Rev 06/2020

PACKAGE/LABEL PRINCIPAL DISPLAY PANEL – 20 mg/5 mL and 40 mg/5 mL

NDC 29273-401-04

FloLipid
simvastatin

20 mg/5 mL

Oral Suspension

IMPORTANT: SHAKE WELL BEFORE USING

For Oral Use Only Discard 30 days after opening

Rx Only

Net Contents:
150 mL

NDC 29273-401-04

FloLipid
simvastatin

20 mg/5 mL

Oral Suspension

IMPORTANT: SHAKE WELL BEFORE USING.

Discard 30 days after opening.

For Oral Use Only

Rx Only

Net Contents: 150 mL

NDC 29273-402-04

FloLipid
simvastatin

40 mg/5 mL

Oral Suspension

IMPORTANT: SHAKE WELL BEFORE USING

For Oral Use Only Discard 30 days after opening

Rx Only

Net Contents:
150 mL

NDC 29273-402-04

FloLipid
simvastatin

40 mg/5 mL

Oral Suspension

IMPORTANT: SHAKE WELL BEFORE USING.

Discard 30 days after opening.

For Oral Use Only

Rx Only

Net Contents: 150 mL